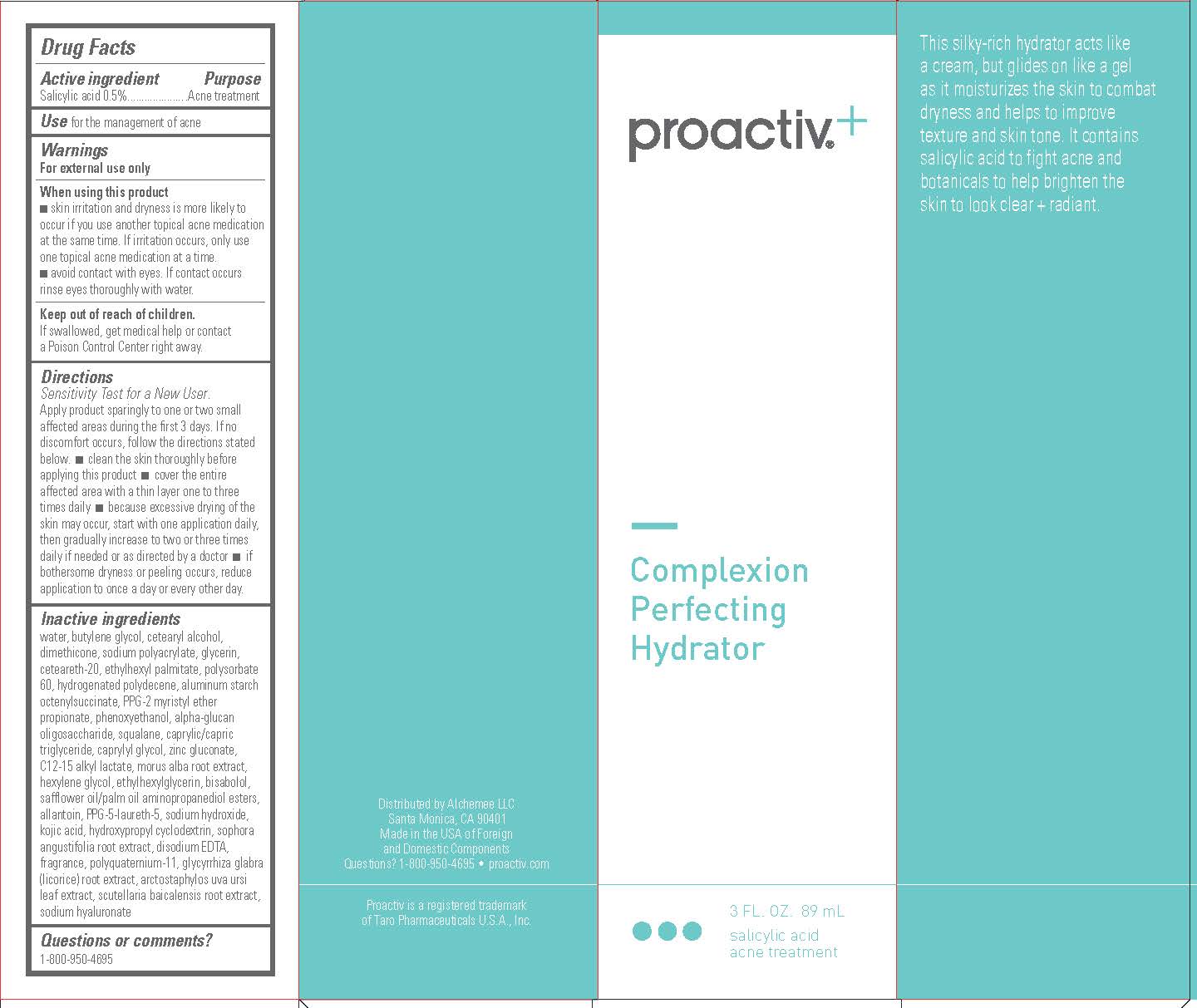 DRUG LABEL: Proactiv Plus Complexion Perfecting Hydrator
NDC: 11410-023 | Form: CREAM
Manufacturer: Alchemee, LLC
Category: otc | Type: HUMAN OTC DRUG LABEL
Date: 20260107

ACTIVE INGREDIENTS: SALICYLIC ACID 0.5 g/100 mL
INACTIVE INGREDIENTS: EDETATE DISODIUM; PHENOXYETHANOL; ADRABETADEX; HYDROGENATED POLYDECENE TYPE I; WATER; BUTYLENE GLYCOL; CETOSTEARYL ALCOHOL; DIMETHICONE; SCUTELLARIA BAICALENSIS ROOT; SOPHORA FLAVESCENS ROOT; MORUS ALBA ROOT; GLYCYRRHIZA GLABRA; ARCTOSTAPHYLOS UVA-URSI LEAF; KOJIC ACID; ZINC GLUCONATE; .ALPHA.-GLUCAN OLIGOSACCHARIDE; HYALURONATE SODIUM; LEVOMENOL; ALLANTOIN; SQUALANE; C12-15 ALKYL LACTATE; MEDIUM-CHAIN TRIGLYCERIDES; CAPRYLYL GLYCOL; SODIUM POLYACRYLATE (8000 MW); ETHYLHEXYLGLYCERIN; GLYCERIN; ETHYLHEXYL PALMITATE; POLYQUATERNIUM-11 (1000000 MW); POLYOXYL 20 CETOSTEARYL ETHER; ALUMINUM STARCH OCTENYLSUCCINATE; POLYSORBATE 60; HEXYLENE GLYCOL; PPG-2 MYRISTYL ETHER PROPIONATE; SODIUM HYDROXIDE

Proactiv+ Complexion Perfecting Hydrator

Drug Facts

Active Ingredient

Salicylic acid 0.5%

Purpose

Acne Treatment

Use

for the management of acne

Warnings

For external use only

When Using this Product

- skin irritation and dryness is more likely to occur if you use another topical acne medication at the same time. If irritation occurs, only use one topical acne medication at a time.
- avoid contact with eyes. If contact occurs, rinse eyes thoroughly with water.

Keep out of reach of children

If swallowed, get medical help or contact a Poison Control Center right away.

Directions

- Sensitivity Test for a New User. Apply product sparingly to one or two small affected areas during the first 3 days. If no discomfort occurs, follow the directions stated below.
- clean the skin thoroughly before applying this product
- cover the entire affected area with a thin layer one to three times daily
- because excessive drying of the skin may occur, start with one application daily, then gradually increase to two or three times daily if needed or as directed by a doctor
- if bothersome dryness or peeling occurs, reduce application to once a day or every other day.

Inactive ingredients

water, butylene glycol, cetearyl alcohol, dimethicone, sodium polyacrylate, glycerin, ceteareth-20, ethylhexyl palmitate, polysorbate 60, hydrogenated polydecene, aluminum starch octenylsuccinate, PPG-2 myristyl ether propionate, phenoxyethanol, alpha-glucan oligosaccharide, squalane, caprylic/capric triglyceride, caprylyl glycol, zinc gluconate, C12-15 alkyl lactate, morus alba root extract, hexylene glycol, ethylhexylglycerin, bisabolol, safflower oil/palm oil aminopropanediol esters, allantoin, PPG-5-laureth-5, sodium hydroxide, kojic acid, hydroxypropyl cyclodextrin, sophora angustifolia root extract, disodium EDTA, fragrance, polyquaternium-11, glycyrrhiza glabra (licorice) root extract, arctostaphylos uva ursi leaf extract, scutellaria baicalensis root extract, sodium hyaluronate

Questions or comments?

1-800-950-4695

PRINCIPAL DISPLAY PANEL - 89 mL

proactiv+

Complexion
Perfecting
Hydrator

3 FL. OZ. 89 mL

salicylic acid
acne treatment